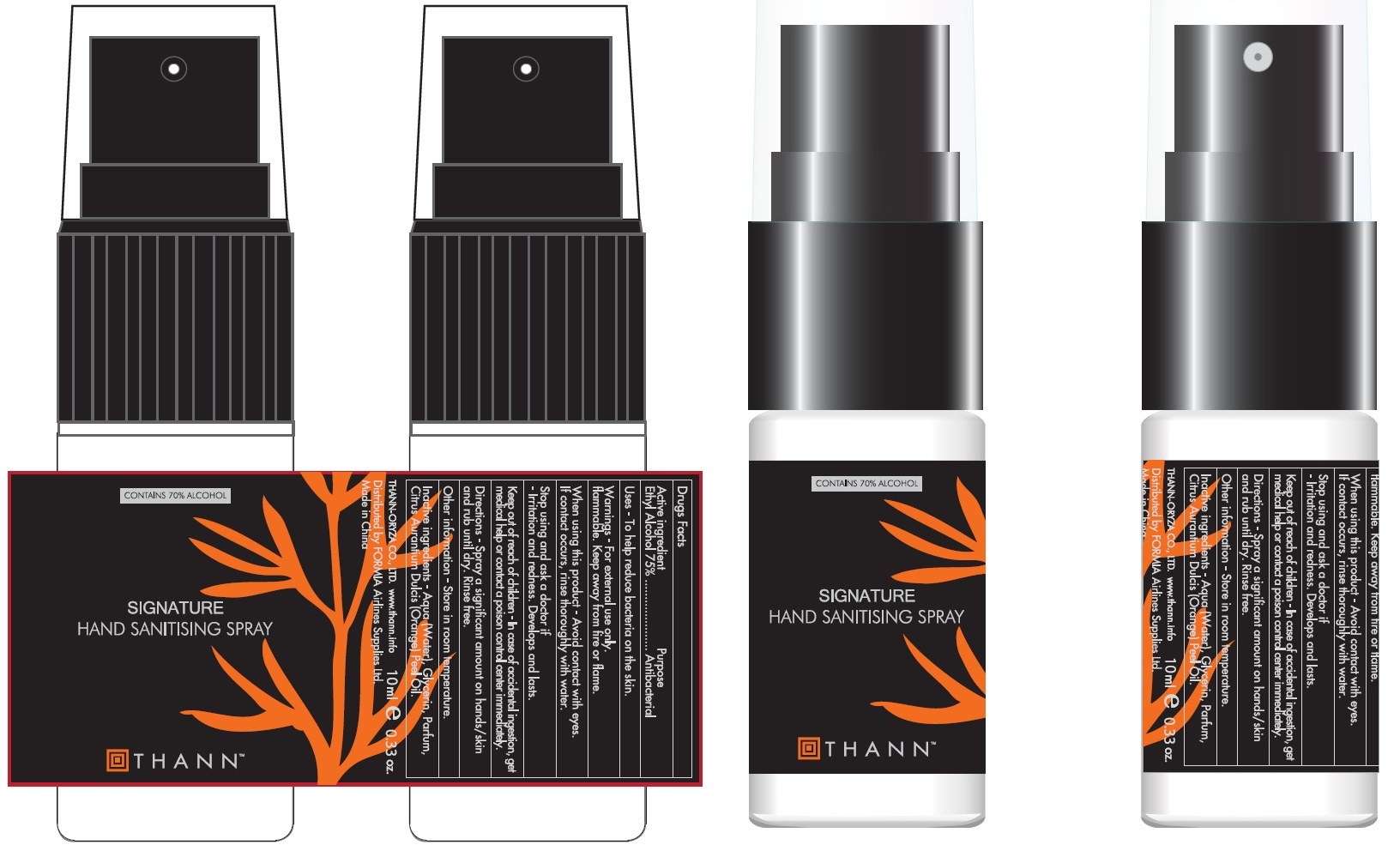 DRUG LABEL: Thann Signature Hand Sanitising
NDC: 79940-002 | Form: LIQUID
Manufacturer: FORMIA Airline Supplies Ltd
Category: otc | Type: HUMAN OTC DRUG LABEL
Date: 20201029

ACTIVE INGREDIENTS: ALCOHOL 0.75 mL/1 mL
INACTIVE INGREDIENTS: WATER; GLYCERIN; ORANGE OIL

Thann Signature Hand Sanitising Spray

Active ingredient

Ethyl Alcohol 75%

Purpose

Antibacterial

Uses

- To help reduce bacteria on the skin.

Warnings

-For external use only.
Flammable. Keep away from fire or flame.

When using this product

-Avoid contact with eyes. If contact occurs, rinse thoroughly with water.

Stop using and ask a doctor if

-Irritation and redness. Develops and lasts.

Keep out of reach of children

-In case of accidental ingestion, get medical help or contact a poison control center immediately.

Directions

-Spray a significant amount on your hand/ skin and rub until fully dry. Rinse free.

Other information

-Store in room temperature.

Inactive ingredients

-Aqua (Water), Glycerin, Parfum (Fragrance), Citrus Aurantium Dulcis (Orange) Peel Oil.